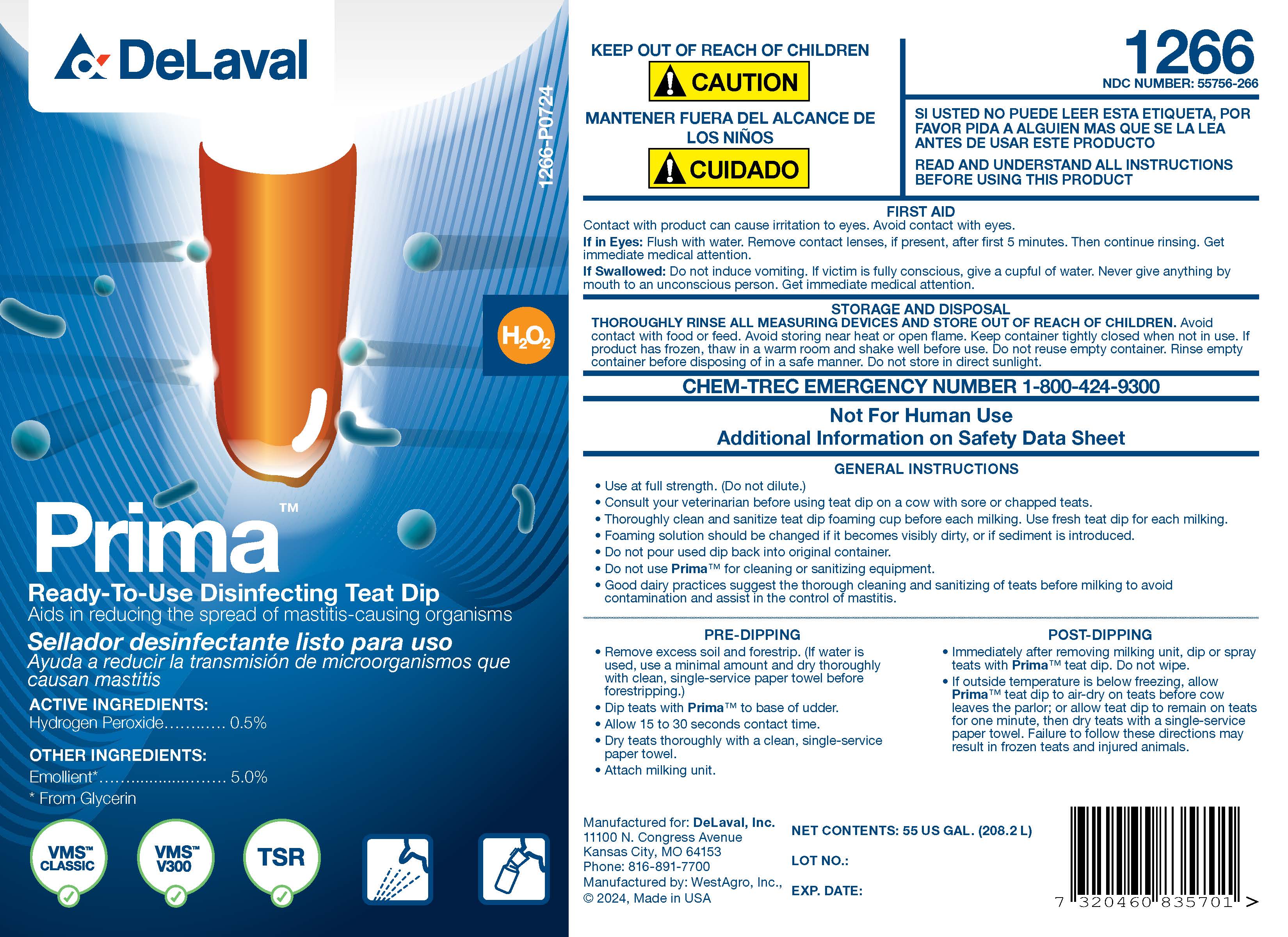 DRUG LABEL: Prima Sanitizing pre and post teat dip
NDC: 55756-266 | Form: SOLUTION
Manufacturer: Delaval
Category: animal | Type: OTC ANIMAL DRUG LABEL
Date: 20240925

ACTIVE INGREDIENTS: Hydrogen Peroxide 5.1 g/1 L

Prima™

PURPOSE

Ready-To-Use Disinfecting Teat Dip

Aids in reducing the spread of mastitis-causing organisms

ACTIVE INGREDIENTS:

Hydrogen Peroxide .................... 0.5%

INACTIVE INGREDIENT

OTHER INGREDIENTS:

Emollient* .................. 5.0%

* From Glycerin

KEEP OUT OF REACH OF CHILDREN

!CAUTION

MANTENER FUERA DEL ALCANCE DE LOST NINOS

!CUIDADO

1266

NDC NUMBER: 55756-266

SI USTED NO PUEDE LEER ESTA ETIQUETA POR FAVOR PIDA A ALGUIEN MAS QUE SE LA LEA ANTES DE USAR ESTE PRODUCTO

READ AND UNDERSTAND ALL INSTRUCTIONS BEFORE USING THIS PRODUCT

FIRST AID
Contact with product can cause irritation to eyes. Avoid contact with eyes.
If in Eyes: Flush with water. Remove contact lenses, if present, after first 5 minutes. Then continue rinsing. Get immediate medical attention.

If Swallowed: Do not induce vomiting. If victim is fully conscious, give a cupful of water. Never give anything by mouth to an unconscious person. Get immediate medical attention.

STORAGE AND DISPOSAL

THOROUGHLY RINSE ALL MEASURING DEVICES AND STORE OUT OF REACH OF CHILDREN. Avoid contact with food or feed. Avoid storing near heat or open flame. Keep container tightly closed when not in use. If product has frozen, store in a warm room and shake well before use. Do not reuse empty container. Rinse empty container before disposing of in a safe manner. Do not store in direct sunlight.

CHEM-TREC EMERGENCY NUMBER 1-800-424-9300

Not for Human Use

Additional Information on Material Safety Data Sheet

INDICATIONS AND USAGE

GENERAL INSTRUCTIONS

- Use at full strength (Do not dilute.)
- Consult your veterinarian before using teat dip on a cow with sore or chapped teats.
- Thoroughly clean and sanitize teat dip foaming cup before each milking. Use fresh teat dip for each milking.
- Foaming solution should be changed if it becomes visibly dirty, or if sediment is introduced.
- Do not pour used dip back into original container.
- Do not use Prima™ for cleaning or sanitizing equipment.
- Good dairy practices suggest the thorough cleaning and sanitizing of teats before milking to avoid contamination and assist in the control of mastitis.

PRE-DIPPING

- Remove excess soil and forestrip. (If water is used, use minimal amount and dry thoroughly with clean, single-service paper towel before forestripping.)
- Dip teats with Prima™ to base of udder.
- Allow 15 to 30 seconds contact time.
- Dry tests thoroughly with a clean, single-service paper towel.
- Attach milking unit.

POST-DIPPING

- Immediately after removing milking unit, dip or spray teats with Prima™ teat dip. Do not wipe.
- If outside temperature is below freezing, allow Prima™ teat dip to air dry on teats before cow leaves the parlor; or allow teat dip to remain on teats for one minute, then dry teats with single-service paper towel. Failure to follow these instructions may result in frozen teats and injured animals.

Manufactured for: DeLaval, Inc.
11100 N. Congress Avenue
Kansas City, MO 64153
Phone: 816-891-7700
Manufactured by: WestAgro, Inc.
©2024, Made in USA

NET CONTENTS:

LOT NO.:

EXP. DATE:

PACKAGE LABEL

Add image transcription here...